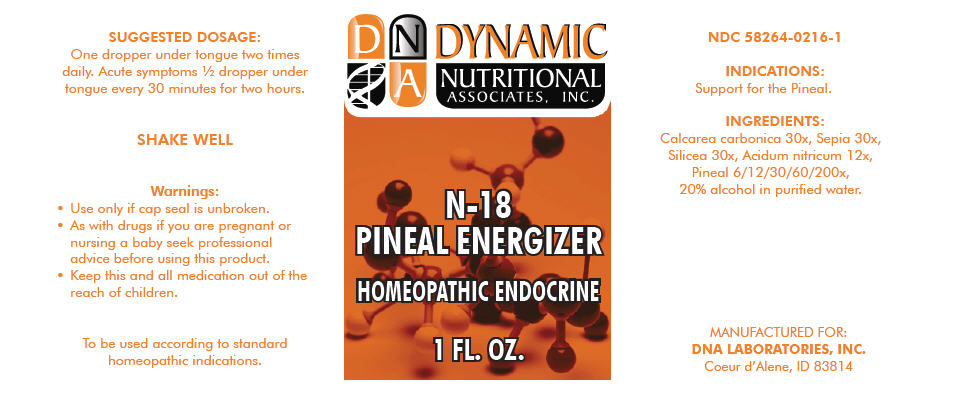 DRUG LABEL: N-18
NDC: 58264-0216 | Form: SOLUTION
Manufacturer: DNA Labs, Inc.
Category: homeopathic | Type: HUMAN OTC DRUG LABEL
Date: 20250109

ACTIVE INGREDIENTS: OYSTER SHELL CALCIUM CARBONATE, CRUDE 30 [hp_X]/1 mL; SEPIA OFFICINALIS JUICE 30 [hp_X]/1 mL; SILICON DIOXIDE 30 [hp_X]/1 mL; NITRIC ACID 12 [hp_X]/1 mL; SUS SCROFA PINEAL GLAND 200 [hp_X]/1 mL
INACTIVE INGREDIENTS: ALCOHOL; WATER

N-18

NDC 58264-0216-1

INDICATIONS

PURPOSE

Support for the Pineal.

INGREDIENTS

INACTIVE INGREDIENT

Calcarea carbonica 30x, Sepia 30x, Silicea 30x, Acidum nitricum 12x, Pineal 6/12/30/60/200x, 20% alcohol in purified water.

SUGGESTED DOSAGE

One dropper under tongue two times daily. Acute symptoms ½ dropper under tongue every 30 minutes for two hours.

STORAGE AND HANDLING

SHAKE WELL

Warnings

- Use only if cap seal is unbroken.

PREGNANCY OR BREAST FEEDING

- As with drugs if you are pregnant or nursing a baby seek professional advice before using this product.

KEEP OUT OF REACH OF CHILDREN

- Keep this and all medication out of the reach of children.

To be used according to standard homeopathic indications.

PRINCIPAL DISPLAY PANEL - 1 FL. OZ. Bottle Label

DYNAMIC
NUTRITIONAL
ASSOCIATES, INC.

N-18
PINEAL ENERGIZER

HOMEOPATHIC ENDOCRINE

1 FL. OZ.